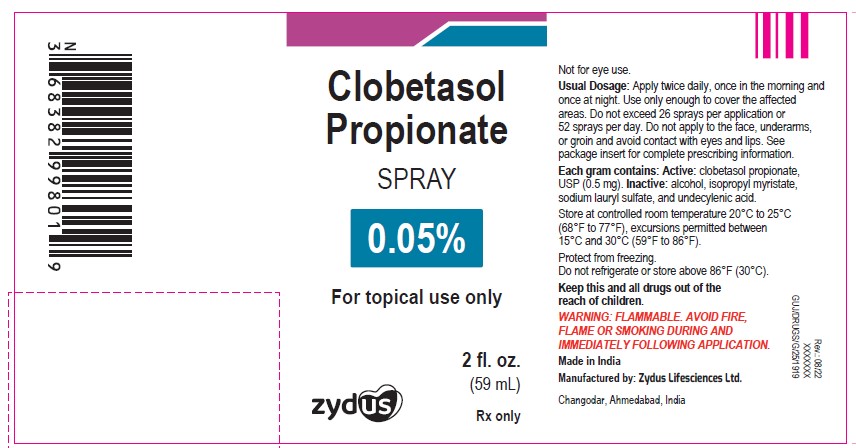 DRUG LABEL: clobetasol propionate
NDC: 70771-1080 | Form: SPRAY
Manufacturer: Zydus Lifesciences Limited
Category: prescription | Type: HUMAN PRESCRIPTION DRUG LABEL
Date: 20241126

ACTIVE INGREDIENTS: CLOBETASOL PROPIONATE 0.05 g/1 mL
INACTIVE INGREDIENTS: ALCOHOL; ISOPROPYL MYRISTATE; SODIUM LAURYL SULFATE; UNDECYLENIC ACID

Clobetasol Propionate Spray, 0.05%

PACKAGE LABEL

Clobetasol Propinate Spray, 0.05%

NDC 70771-1080-6

2 fl. oz. (59 mL)